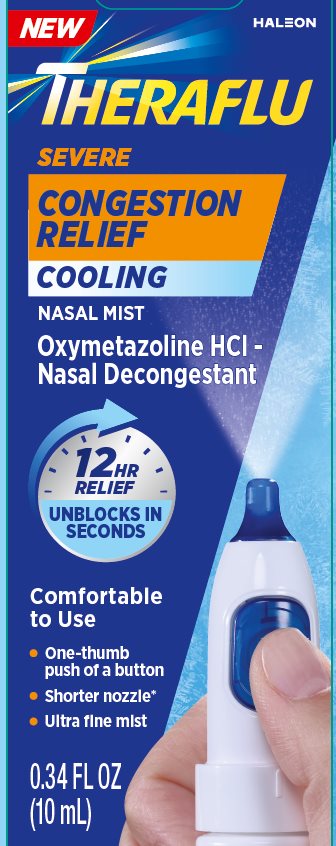 DRUG LABEL: Theraflu
NDC: 0067-0109 | Form: SPRAY
Manufacturer: Haleon US Holdings LLC
Category: otc | Type: HUMAN OTC DRUG LABEL
Date: 20250717

ACTIVE INGREDIENTS: OXYMETAZOLINE HYDROCHLORIDE .5 mg/1 mL
INACTIVE INGREDIENTS: BENZALKONIUM CHLORIDE; EDETATE DISODIUM; EUCALYPTOL; MENTHOL, UNSPECIFIED FORM; POLYOXYL 40 HYDROGENATED CASTOR OIL; WATER; SODIUM CHLORIDE; SODIUM PHOSPHATE, DIBASIC, ANHYDROUS; SODIUM PHOSPHATE, MONOBASIC, UNSPECIFIED FORM; SORBITOL

Drug Facts

Active ingredient

Oxymetazoline HCl 0.05%

Purpose

Nasal decongestant

Uses

- temporarily relieves nasal decongestion due to:
  - common cold
  - hay fever or other upper respiratory allergies (allergic rhinitis)
- temporarily relieves stuffy nose
- helps clear nasal passages; shrinks swollen membranes
- temporarily restores freer breathing through the nose
- helps decongest sinus openings and passages; temporarily relieves sinus congestion and pressure

Warnings

Ask a doctor before use if you have

- heart disease
- high blood pressure
- thyroid disease
- diabetes
- trouble urinating due to an enlarged prostate gland

When using this product

- do not exceed recommended dosage
- do not use this product for more than 3 days. Use only as directed. Frequent or prolonged use may cause nasal congestion to recur or worsen. If symptoms persist, consult a doctor.
- temporary discomfort such as burning, stinging, sneezing, or an increase in nasal discharge may occur
- the use of this container by more than one person may spread infection

Stop use and ask a doctor if

symptoms persist

If pregnant or breast-feeding,

ask a health professional before use.

Keep out of reach of children.

If swallowed, get medical help or contact a Poison Control center right away.

Directions

- do not use more than directed
- adults and children 6 years to under 12 years of age (with adult supervision): 2 sprays in each nostril not more often than every 10 to 12 hours. Do not exceed 2 doses in any 24-hour period.
- children under 6 years of age: consult a doctor

To Use: Shake well before use. To remove the cap, press grooves on each side and turn to lift cap. Before using the first time, prime the sprayer by pressing the button several times. To spray, insert sprayer tip into nostril, firmly press the button with thumb and sniff deeply. Stay upright while spraying. Wipe sprayer tip clean and secure cap after use.

Other information

- do not store above 25°C (77°F)

Inactive ingredients

benzalkonium chloride solution, edetate disodium, eucalyptol, menthol, polyoxyl 40 hydrogenated castor oil, purified water, sodium chloride, sodium phosphate dibasic, sodium phosphate monobasic, sorbitol

Questions?

1-855-328-5259

Additional Information

READ ALL WARNINGS AND DIRECTIONS ON CARTON BEFORE USE. KEEP CARTON FOR REFERENCE. DO NOT DISCARD.

Breathe Better at the Push of a Button

1. Find grooves on each side of cap

2. Press grooves and turn to lift cap

3. Press firmly with thumb

Do not use if red unlock icon is seen on either end of the carton before first opening or if the red unlock icon is absent after opening.

*vs. the leading nasal mist

Package/Label Principal Display Panel

NEW

THERAFLU

SEVERE

CONGESTION RELIEF

COOLING

NASAL MIST

Oxymetazoline HCl –

Nasal Decongestant

12 HR RELIEF

UNBLOCKS IN SECONDS

Comfortable to use

- One-thumb push of a button
- Shorter nozzle*
- Ultra fine mist

0.34 FL OZ (10 mL)